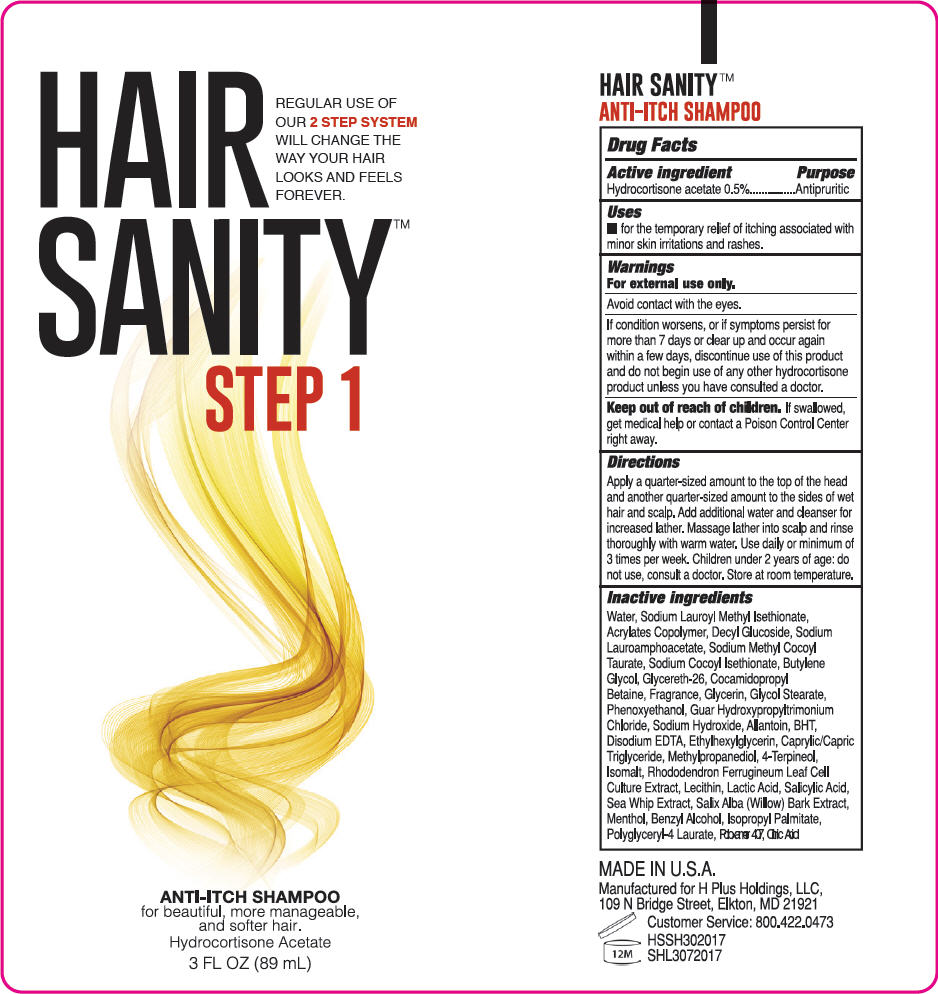 DRUG LABEL: HairSanity Step 1
NDC: 71605-000 | Form: SHAMPOO
Manufacturer: H Plus Holdings
Category: otc | Type: HUMAN OTC DRUG LABEL
Date: 20170726

ACTIVE INGREDIENTS: HYDROCORTISONE ACETATE 5 mg/1 mL
INACTIVE INGREDIENTS: SODIUM LAUROYL METHYL ISETHIONATE; METHACRYLIC ACID - ETHYL ACRYLATE COPOLYMER (4500 MPA.S); DECYL GLUCOSIDE; SODIUM LAUROAMPHOACETATE; SODIUM METHYL COCOYL TAURATE; SODIUM COCOYL ISETHIONATE; BUTYLENE GLYCOL; GLYCERETH-26; COCAMIDOPROPYL BETAINE; GLYCERIN; GLYCOL STEARATE; PHENOXYETHANOL; SODIUM HYDROXIDE; GUAR HYDROXYPROPYLTRIMONIUM CHLORIDE (1.7 SUBSTITUENTS PER SACCHARIDE); ALLANTOIN; BUTYLATED HYDROXYTOLUENE; EDETATE DISODIUM; ETHYLHEXYLGLYCERIN; MEDIUM-CHAIN TRIGLYCERIDES; METHYLPROPANEDIOL; 4-TERPINEOL, (+)-; LECITHIN, SOYBEAN; ISOPROPYL PALMITATE; POLOXAMER 407; ISOMALT; SALICYLIC ACID; PSEUDOPTEROGORGIA ELISABETHAE; SALIX ALBA BARK; MENTHOL, UNSPECIFIED FORM; BENZYL ALCOHOL; RHODODENDRON FERRUGINEUM LEAF; LACTIC ACID, UNSPECIFIED FORM; WATER; CITRIC ACID MONOHYDRATE

HairSanity™ Step 1

Drug Facts

Active ingredient

Hydrocortisone acetate 0.5%

Purpose

Antipruritic

Uses

- for the temporary relief of itching associated with minor skin irritations and rashes.

Warnings

For external use only.

Avoid contact with the eyes.

If condition worsens, or if symptoms persist for more than 7 days or clear up and occur again within a few days, discontinue use of this product and do not begin use of any other hydrocortisone product unless you have consulted a doctor.

Keep out of reach of children. If swallowed, get medical help or contact a Poison Control Center right away.

Directions

Apply a quarter-sized amount to the top of the head and another quarter-sized amount to the sides of wet hair and scalp. Add additional water and cleanser for increased lather. Massage lather into scalp and rinse thoroughly with warm water. Use daily or minimum of 3 times per week. Children under 2 years of age: do not use, consult a doctor. Store at room temperature.

Inactive ingredients

Water, Sodium Lauroyl Methyl Isethionate, Acrylates Copolymer, Decyl Glucoside, Sodium Lauroamphoacetate, Sodium Methyl Cocoyl Taurate, Sodium Cocoyl Isethionate, Butylene Glycol, Glycereth-26, Cocamidopropyl Betaine, Fragrance, Glycerin, Glycol Stearate, Phenoxyethanol, Guar Hydroxypropyltrimonium Chloride, Sodium Hydroxide, Allantoin, BHT, Disodium EDTA, Ethylhexylglycerin, Caprylic/Capric Triglyceride, Methylpropanediol, 4-Terpineol, Isomalt, Rhododendron Ferrugineum Leaf Cell Culture Extract, Lecithin, Lactic Acid, Salicylic Acid, Sea Whip Extract, Salix Alba (Willow) Bark Extract, Menthol, Benzyl Alcohol, Isopropyl Palmitate, Polyglyceryl-4 Laurate, Poloxamer 407, Citric Acid

PRINCIPAL DISPLAY PANEL - 89 mL Tube Label

HAIR
SANITY™
STEP 1

REGULAR USE OF
OUR 2 STEP SYSTEM
WILL CHANGE THE
WAY YOUR HAIR
LOOKS AND FEELS
FOREVER.

ANTI-ITCH SHAMPOO
for beautiful, more manageable,
and softer hair.
Hydrocortisone Acetate

3 FL OZ (89 mL)